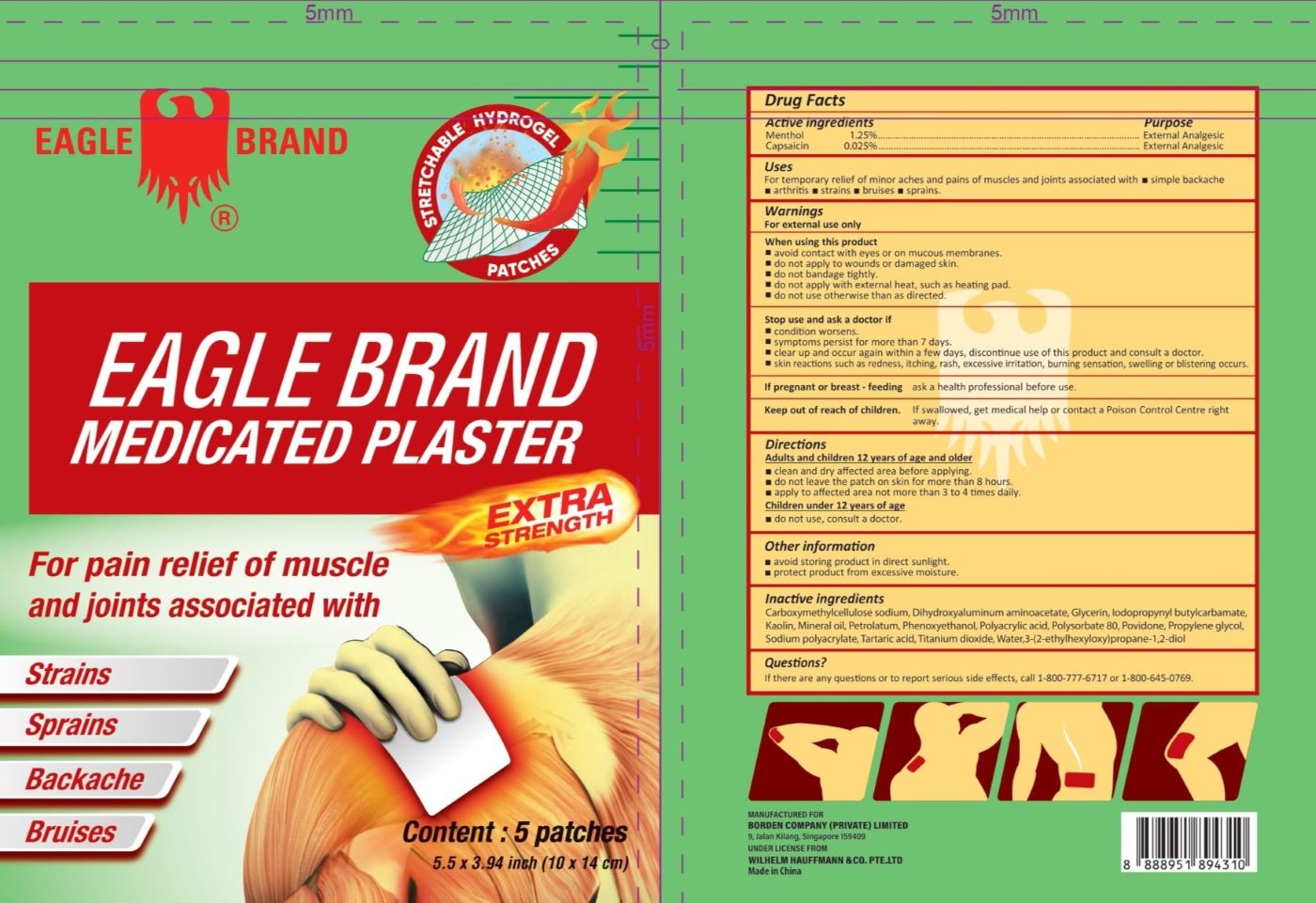 DRUG LABEL: Eagle Brand
NDC: 43405-301 | Form: PATCH
Manufacturer: Borden Company (Private) Limited
Category: otc | Type: HUMAN OTC DRUG LABEL
Date: 20250310

ACTIVE INGREDIENTS: CAPSAICIN 0.025 g/100 g; MENTHOL 1.25 g/100 g
INACTIVE INGREDIENTS: TITANIUM DIOXIDE; POLYACRYLIC ACID (8000 MW); GLYCERIN; POLYSORBATE 80; PETROLATUM; CARBOXYMETHYLCELLULOSE SODIUM; SODIUM POLYACRYLATE (2500000 MW); TARTARIC ACID, D-; MINERAL OIL; KAOLIN; IODOPROPYNYL BUTYLCARBAMATE; DIHYDROXYALUMINUM AMINOACETATE; PHENOXYETHANOL; WATER; PROPYLENE GLYCOL; POVIDONE; ETHYLHEXYLGLYCERIN

Eagle Brand Medicated Plaster Extra Strength

Active ingredients

- Menthol 1.25%
- Capsaicin 0.025%

Purpose

External Analgesic

Uses

For temporary relief of minor aches and pains of muscles and joints associated with ▪ simple backache ▪ arthritis ▪ strains ▪ bruises ▪ sprains.

Warnings

For external use only

When using this product

▪ Avoid contact with eyes or on mucous membranes.

▪ Do not apply to wounds or damaged skin.

▪ Do not bandage tightly.

▪ Do not apply wiht external heat, such as heating pad.

▪ Do not use otherwise than as directed

Stop use and ask doctor if

▪ Condition worsens.

▪ Symptoms persist for more than 7 days.

▪ Clear up and occur again within a few days, discontinue use of this product and consult a doctor.

▪ Skin reactions such as redness, itching, rash, excessive irritation, burning sensation, swelling or blistering occurs.

If pregnant or breast-feeding

Ask a health professional before use.

Keep out of reach of children

If swallowed, get medical help or contact a Poison Control Centre right away.

Directions

Adults and children 12 years of age and above:

▪ Clean and dry affected area before applying.

▪ Do not leave the patch on skin for more than 8 hours.

▪ Apply to affected area not more than 3 to 4 times daily.

Children under 12 years of age:

▪ Do not use, consult a doctor.

Other information

▪ Avoid storing product in direct sunlight.

▪ Protect product from excessive moisture.

Inactive ingredients

Carboxymethylcellulose sodium, Dihydroxyaluminum aminoacetate, Glycerin, Iodopropynyl butylcarbamate, Kaolin, Mineral oil, Petrolatum, Phenoxyethanol, Polyacrylic acid, Polysorbate, Povidone, Propylene glycol, Sodium polyacrylate, Tartaric acid, Titanium dioxide, Water, 3-(2-ethylhexyloxy)propane-1,2-diol

Questions?

If there are any questions or to report serious side effects, call 1-800-777-6717 or 1-800-645-0769.

Package Label

5 Patches in 1 Pouch NDC: 43405-301-05